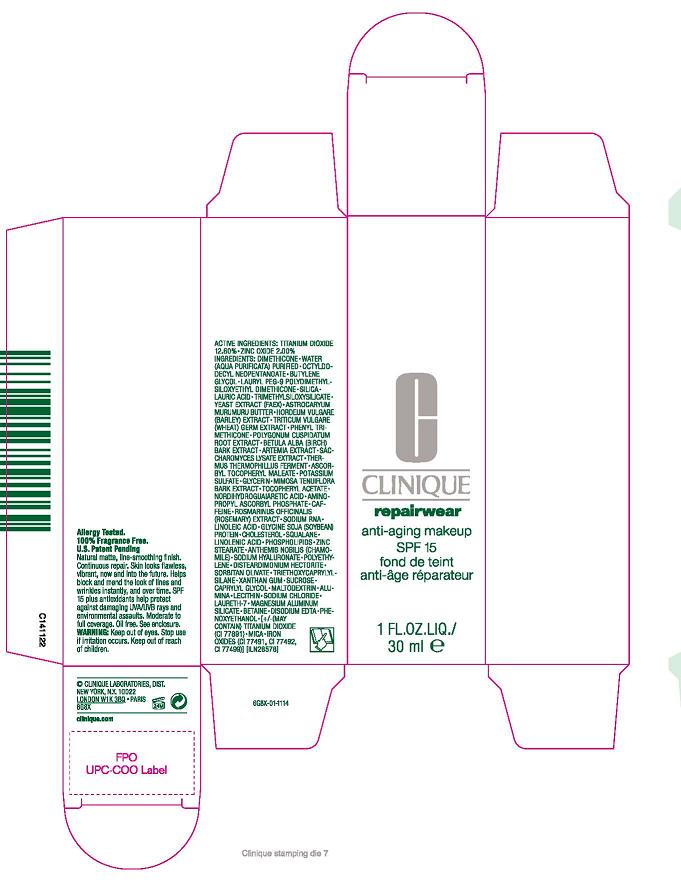 DRUG LABEL: REPAIRWEAR ANTI -AGING MAKEUP
NDC: 49527-920 | Form: CREAM
Manufacturer: CLINIQUE LABORATORIES INC.
Category: otc | Type: HUMAN OTC DRUG LABEL
Date: 20100323

ACTIVE INGREDIENTS: titanium dioxide 12.6 mL/100 mL; zinc oxide 2.0 mL/100 mL

PACKAGE LABEL

CLINIQUE
REPAIRWEAR ANTI-AGING MAKEUP SPF 15
1 FL.OZ. LIQ./ 30 ML
CLINIQUE LABORATORIES INC, DIST.
NEW YORK, NY 10022

ACTIVE INGREDIENT

ACTIVE INGREDIENTS: TITANIUM DIOXIDE 12.6%, ZINC OXIDE 2.0%

WARNINGS

WARNINGS: KEEP OUT OF EYES. STOP USE IF IRRITATION OCCURS.KEEP OUT OF REACH OF CHILDREN.